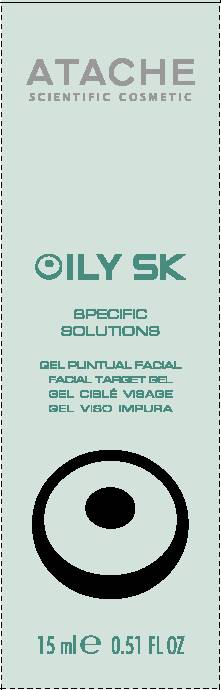 DRUG LABEL: Oily SK Specific Solutions
NDC: 75870-007 | Form: GEL
Manufacturer: LABORATORIOS DE COSMETICA SCIENTIFICA ATACHE 
Category: otc | Type: HUMAN OTC DRUG LABEL
Date: 20110621

ACTIVE INGREDIENTS: SALICYLIC ACID .06 mL/15 mL
INACTIVE INGREDIENTS: WATER; ALCOHOL; GLYCERIN; CAPRYLOYL GLYCINE; MALIC ACID; SODIUM SALICYLATE; CHLORHEXIDINE GLUCONATE; ALMOND; PLANTAGO LANCEOLATA LEAF; ZINC PIDOLATE; MAHONIA AQUIFOLIUM ROOT BARK; BUTYLENE GLYCOL; SODIUM HYDROXIDE

DRUG FACTS

PURPOSE
Acne treatment

INDICATIONS AND USAGE

INDICATIONS AND INSTRUCTIONS FOR USE: When blemish appears, apply directly on the affected area. Use twice a day until the disappearance of the blemish.

WARNINGS

WARNINGS: For external use only. Avoid contact with the eyes and mucous membranes. Discontinue use if signs of irritation or rash appear.

ACTIVE INGREDIENT:

Salicylic Acid - .40% - Purpose: acne treatment

INACTIVE INGREDIENT

COSMETIC INGREDIENTS: WATER, ALCOHOL DENAT., GLYCERIN, HYDROXYETHYL ETHYLCELLULOSE, CAPRYLOYL GLYCINE, MALIC ACID, SODIUM SALICYLATE, CHLORHEXIDINE DIGLUCONATE, HYDROLYZED SWEET ALMOND PROTEIN, PLANTAGO LANCEOLATA LEAF EXTRACT, ZINC PCA, BERBERIS AQUIFOLIUM EXTRACT, BUTYLENE GLYCOL, SODIUM HYDROXIDE.

Keep out of reach of children.

DOSAGE AND ADMINISTRATION

INSTRUCTIONS FOR USE: Squeeze a small amount onto the affected area twice a day until the blemish is gone.